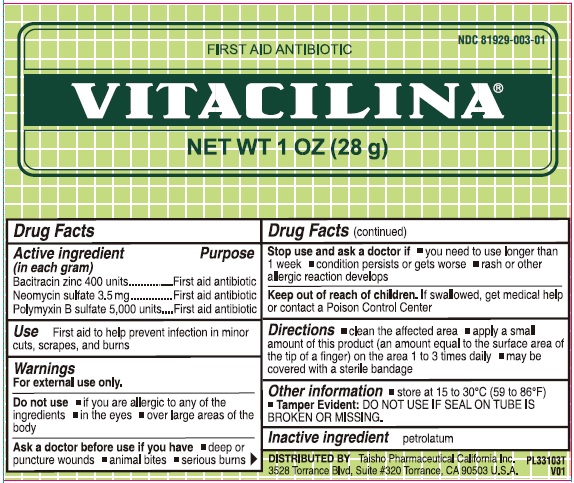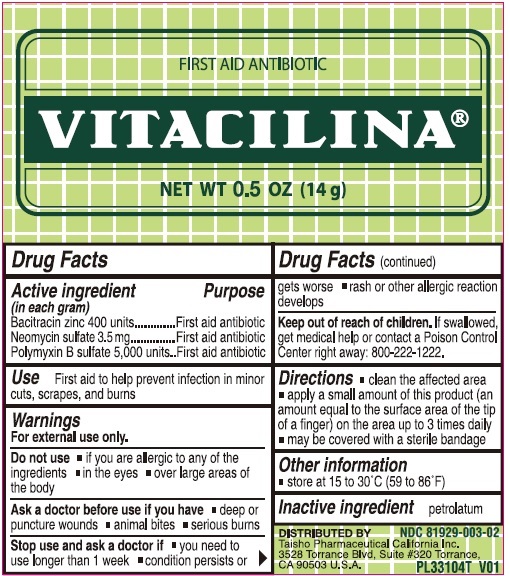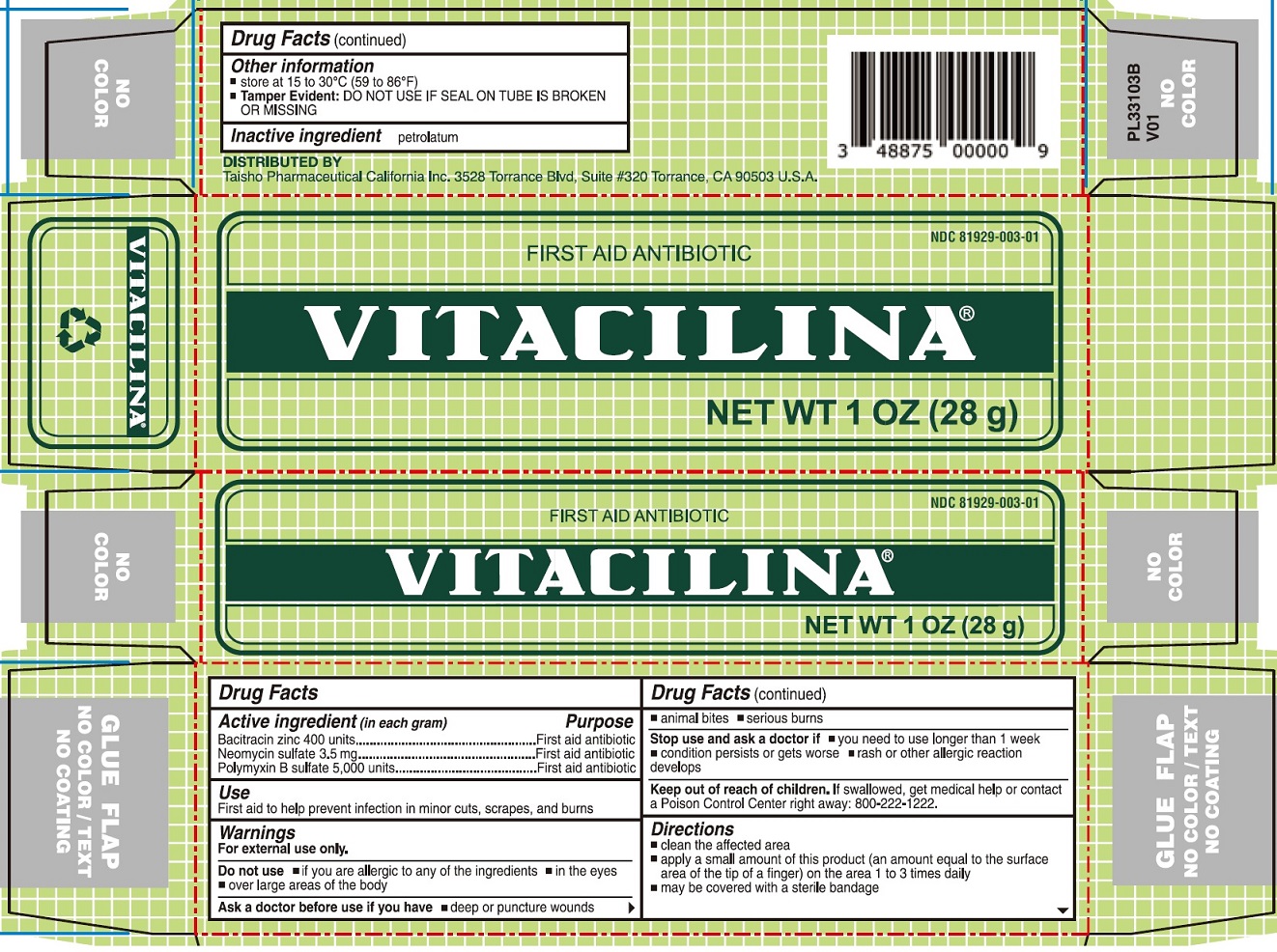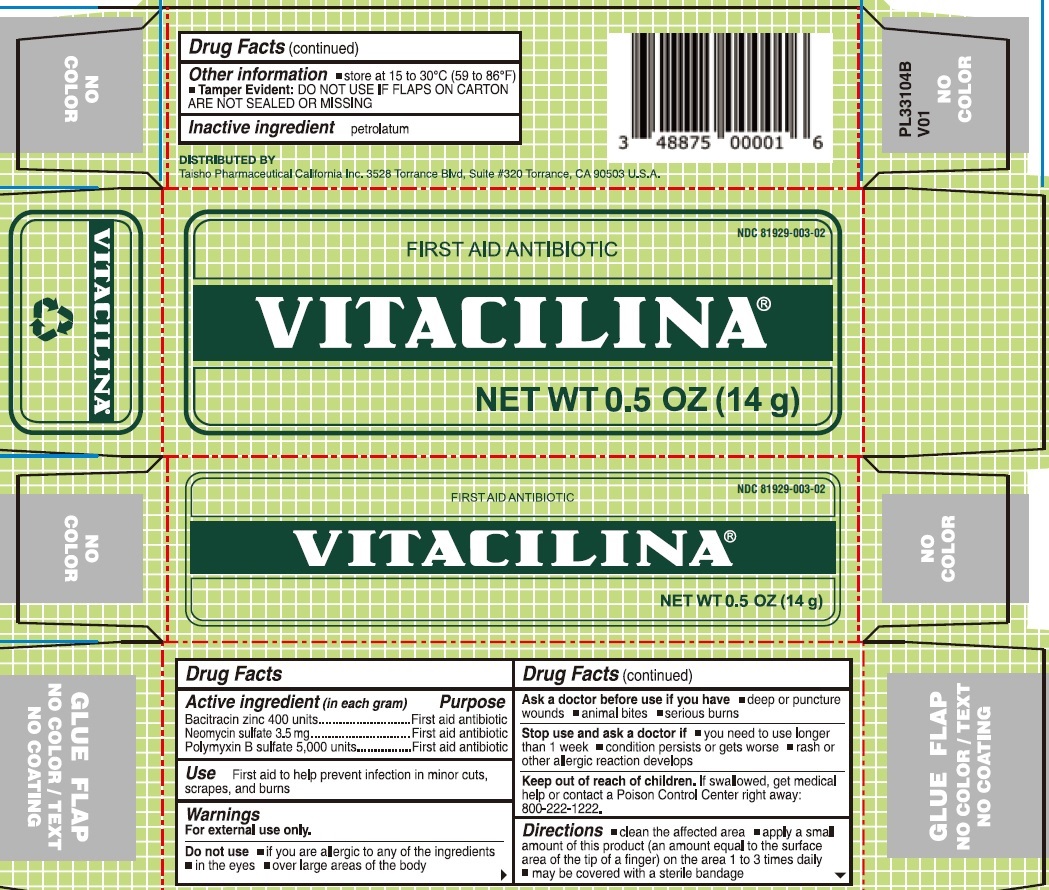 DRUG LABEL: Vitacilina First Aid Antibiotic
NDC: 81929-003 | Form: OINTMENT
Manufacturer: Taisho Pharmaceutical California Inc.
Category: otc | Type: HUMAN OTC DRUG LABEL
Date: 20250807

ACTIVE INGREDIENTS: BACITRACIN ZINC 400 U/1 g; NEOMYCIN SULFATE 3.5 mg/1 g; POLYMYXIN B SULFATE 5000 U/1 g
INACTIVE INGREDIENTS: PETROLATUM

Vitacilina First Aid Antibiotic

Active ingredient (in each gram)

Bacitracin Zinc 400 units

Neomycin sulfate 3.5 mg

Polymyxin B sulfate 5,000 units

Purpose

First aid antibiotic

Use

First aid to help prevent infection in minor cuts, scrapes, and burns

Warnings

For external use only.

Do not use

- if you are allergic to any of the ingredients
- in the eyes
- over large areas of the body

Ask a doctor before use if you have

- deep or puncture wounds
- animal bites
- serious burns

Stop use and ask a doctor if

- you need to use longer than 1 week
- condition persists to gets worse
- rash or other allergic reaction develops

Keep out of reach of children.

If swallowed, get medical help or contact a Poison Control Center

Directions

- clean the affected area
- apply a small amount of this product (an amount equal to the surface area of the tip of a finger) on the area 1 to 3 times daily
- may be covered with a sterile bandage

Other information

- store at 15 to 30°C (59 to 86°F)
- DO NOT USE IF SEAL ON TUBE IS BROKEN OR MISSING. Tamper Evident:

Inactive ingredient

petrolatum

Package Labeling 28g

Add image transcription here...

Add image transcription here...